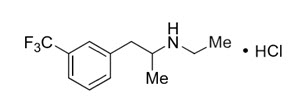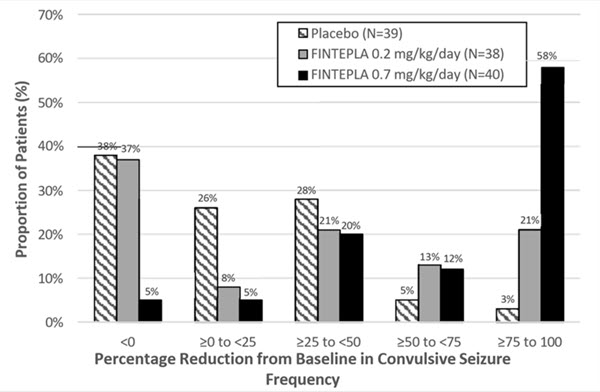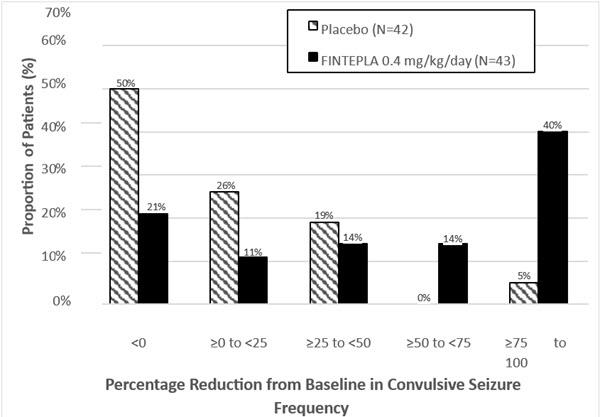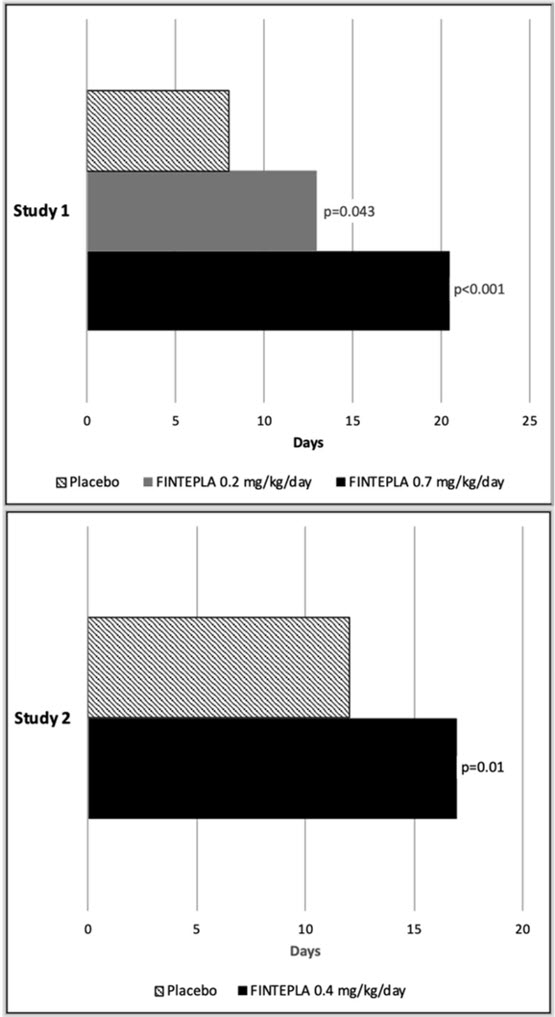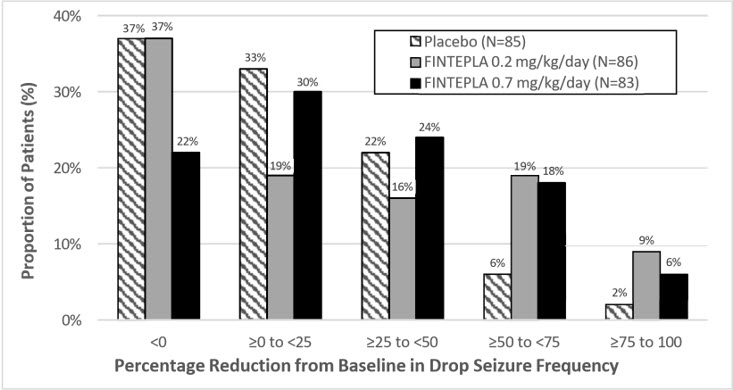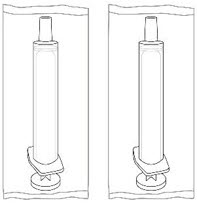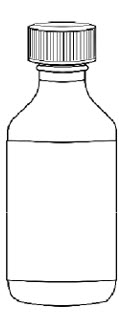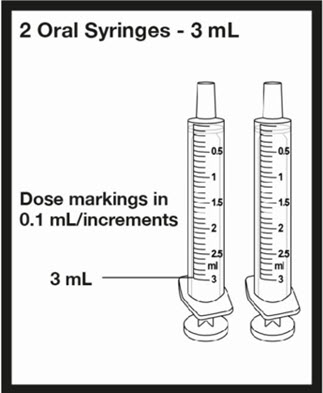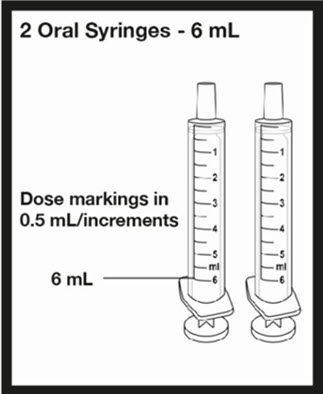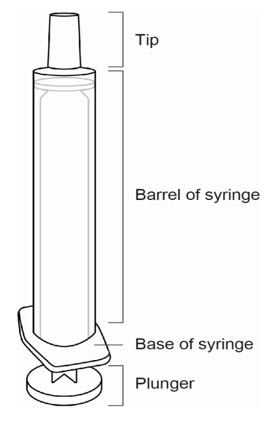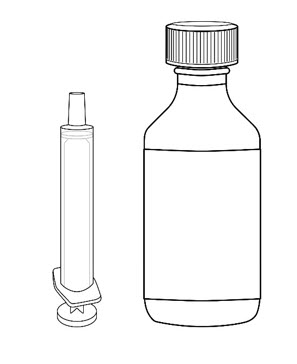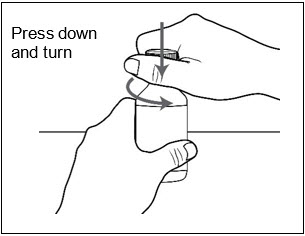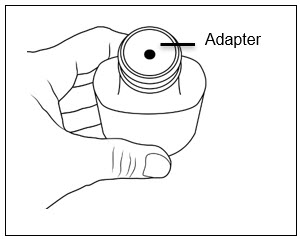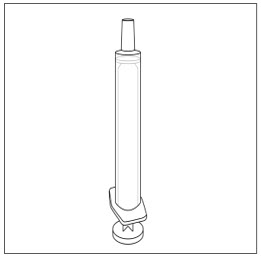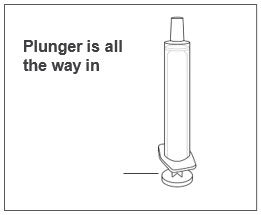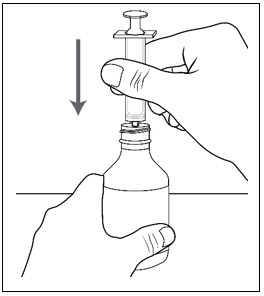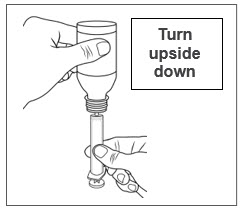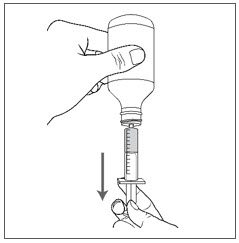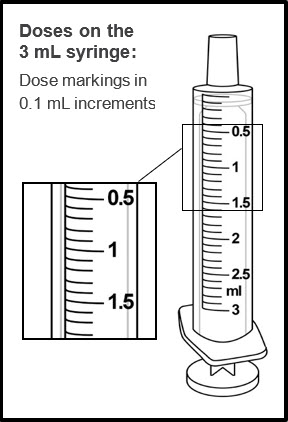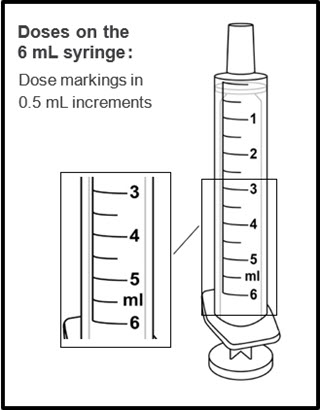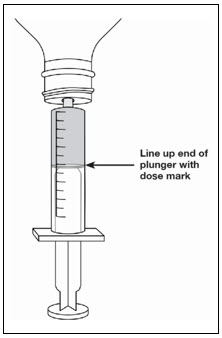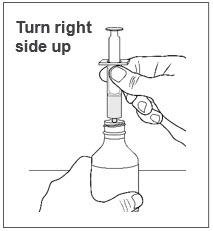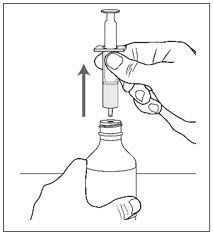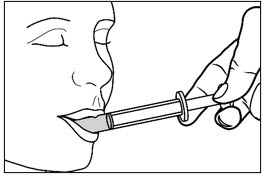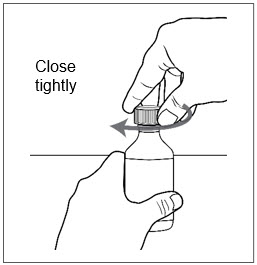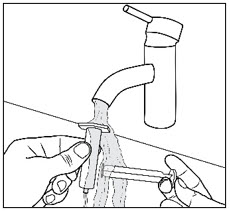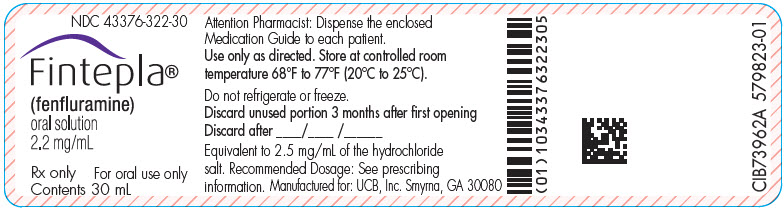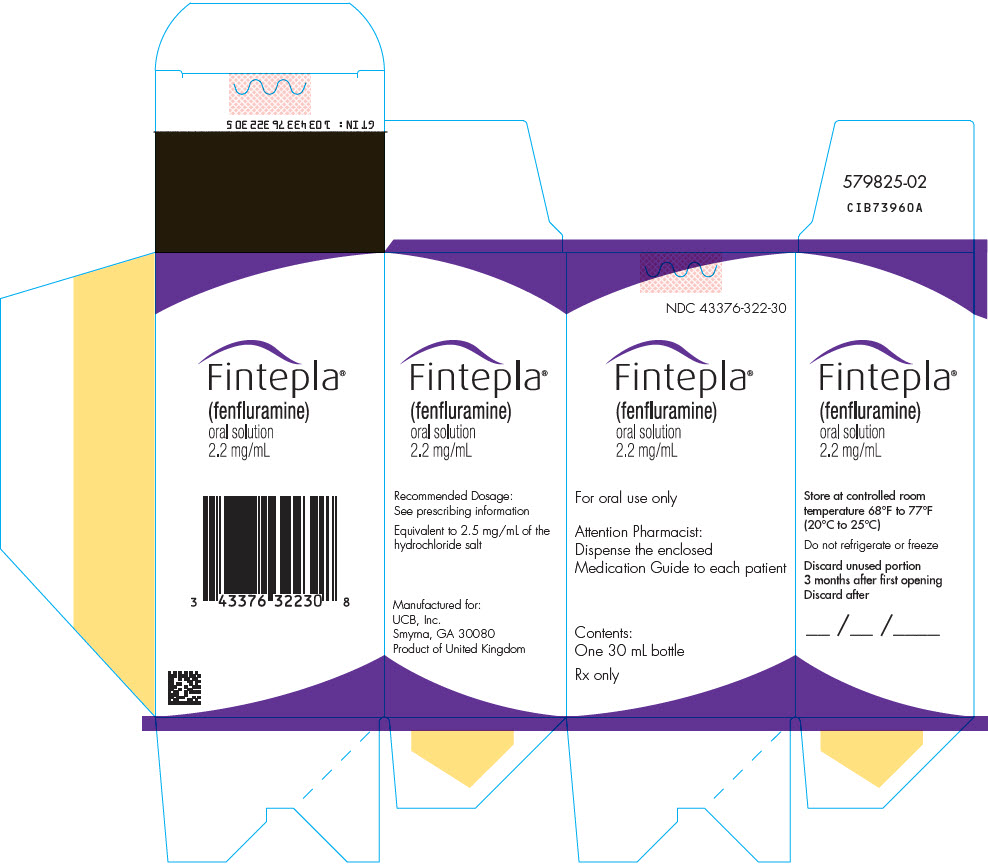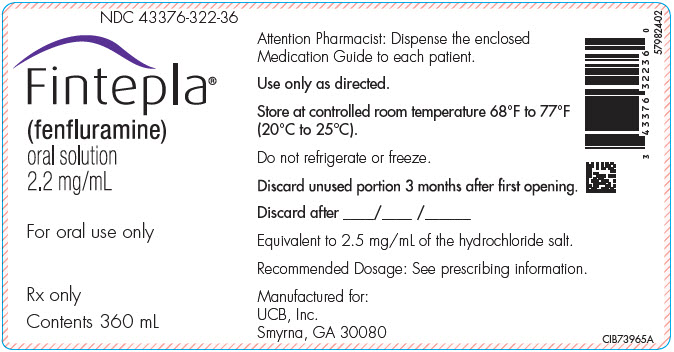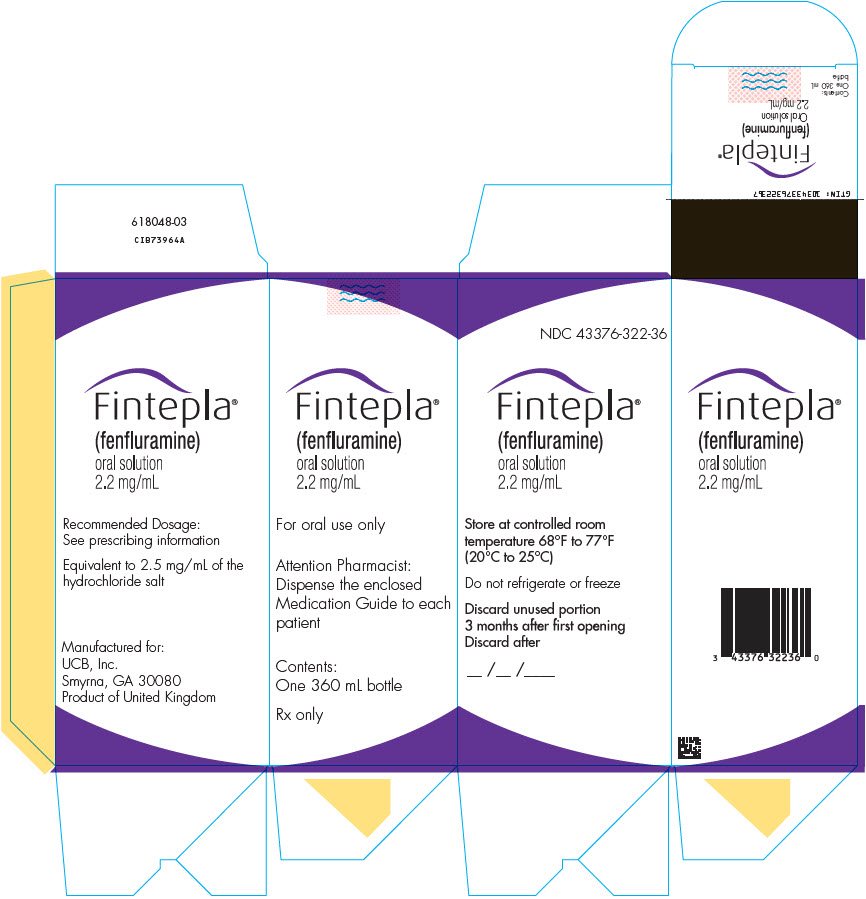 DRUG LABEL: Fintepla
NDC: 43376-322 | Form: SOLUTION
Manufacturer: UCB, Inc.
Category: prescription | Type: HUMAN PRESCRIPTION DRUG LABEL
Date: 20251027

ACTIVE INGREDIENTS: FENFLURAMINE 2.2 mg/1 mL
INACTIVE INGREDIENTS: WATER; POTASSIUM CITRATE; ANHYDROUS CITRIC ACID; HYDROXYETHYL CELLULOSE (2000 MPA.S AT 1%); METHYLPARABEN; SUCRALOSE; ETHYLPARABEN

HIGHLIGHTS OF PRESCRIBING INFORMATION

These highlights do not include all the information needed to use FINTEPLA safely and effectively. See full prescribing information for FINTEPLA.
FINTEPLA®(fenfluramine) oral solution
Initial U.S. Approval: 1973

WARNING: VALVULAR HEART DISEASE and PULMONARY ARTERIAL HYPERTENSION

See full prescribing information for complete boxed warning.

- FINTEPLA can cause valvular heart disease and pulmonary arterial hypertension. (5.1)
- Echocardiogram assessments are required before, during, and after treatment with FINTEPLA. (2.1, 2.6, 5.1)
- FINTEPLA is available only through a restricted program called the FINTEPLA REMS. (5.2)

RECENT MAJOR CHANGES

Boxed Warning | 4/2025
Warnings and Precautions (5.1) | 4/2025

1 INDICATIONS AND USAGE

FINTEPLA is indicated for the treatment of seizures associated with Dravet syndrome and Lennox-Gastaut syndrome in patients 2 years of age and older. (1)

2 DOSAGE AND ADMINISTRATION

- FINTEPLA is to be administered orally and may be taken with or without food. (2.2)
- Dravet Syndrome
  - The initial starting and maintenance dosage is 0.1 mg/kg twice daily, which can be increased weekly based on efficacy and tolerability. (2.2)
  - The maximum daily maintenance dosage of FINTEPLA is 0.35 mg/kg twice daily (maximum daily dosage of 26 mg). (2.2)
- Lennox-Gastaut Syndrome
  - The initial starting dosage is 0.1 mg/kg twice daily, which should be
    increased weekly based on tolerability. (2.2)
  - The recommended maintenance dosage of FINTEPLA is 0.35 mg/kg twice daily (maximum daily dosage of 26 mg). (2.2)
- Dravet Syndrome and Lennox-Gastaut Syndrome
  - Dose adjustment is required in patients taking concomitant stiripentol plus clobazam: the maximum daily maintenance dosage of FINTEPLA is 0.2 mg/kg twice daily (maximum daily dosage of 17 mg). (2.2, 2.3, 2.4, 7.1)
- Dosage adjustment is recommended in patients:
  - Taking strong CYP1A2 or CYP2D6 inhibitors (2.3, 7.1)
  - With severe renal impairment (2.4, 8.6)
  - With mild, moderate, and severe hepatic impairment (2.5, 8.7)

3 DOSAGE FORMS AND STRENGTHS

Oral solution: 2.2 mg/mL fenfluramine (3)

4 CONTRAINDICATIONS

- Hypersensitivity to fenfluramine or any of the excipients in FINTEPLA (4)
- Within 14 days of the administration of monoamine oxidase inhibitors due to an increased risk of serotonin syndrome (4)

5 WARNINGS AND PRECAUTIONS

- Decreased Appetite and Decreased Weight: Advise patients that FINTEPLA can cause decreased appetite and decreased weight. (5.3)
- Somnolence, Sedation, and Lethargy: Monitor for somnolence and sedation. Advise patients not to drive or operate machinery until they have gained sufficient experience on FINTEPLA. (5.4)
- Suicidal Behavior and Ideation: Monitor patients for suicidal behavior and thoughts. (5.5)
- Withdrawal of Antiepileptic Drugs: FINTEPLA should be gradually withdrawn to minimize the risk of increased seizure frequency and status epilepticus. (5.6)
- Serotonin Syndrome: Advise patients that serotonin syndrome is a potentially life-threatening condition and may occur with FINTEPLA, particularly with concomitant administration of FINTEPLA with other serotonergic drugs. (5.7)
- Increase in Blood Pressure: Monitor blood pressure during treatment. (5.8)
- Glaucoma: Discontinue therapy in patients with acute decrease in visual acuity or ocular pain. (5.9)

6 ADVERSE REACTIONS

The most common adverse reactions (incidence at least 10% and greater than placebo) in patients with Dravet syndrome were decreased appetite; somnolence, sedation, lethargy; diarrhea; constipation; abnormal echocardiogram; fatigue, malaise, asthenia; ataxia, balance disorder, gait disturbance; blood pressure increased; drooling, salivary hypersecretion; pyrexia; upper respiratory tract infection; vomiting; decreased weight; fall; status epilepticus. (6.1)

The most common adverse reactions (incidence at least 10% and greater than placebo) in patients with Lennox-Gastaut syndrome were diarrhea; decreased appetite; fatigue; somnolence; vomiting. (6.1)

To report SUSPECTED ADVERSE REACTIONS, contact UCB, Inc. at 1-844-599-2273 or FDA at 1-800-FDA-1088 or www.fda.gov/medwatch.

7 DRUG INTERACTIONS

- Dose adjustment is required for patients taking stiripentol plus clobazam. (2.2, 2.3, 7.1)
- Strong CYP1A2 or CYP2D6 inhibitors: a dose adjustment is recommended (2.3, 7.1)
- Strong CYP1A2, CYP2B6, or CYP3A4 inducers: it is recommended to avoid coadministration with FINTEPLA. If coadministration is necessary, consider a FINTEPLA dosage increase. (7.1)

8 USE IN SPECIFIC POPULATIONS

- Pregnancy: Based on animal data, may cause fetal harm (8.1)

FULL PRESCRIBING INFORMATION

WARNING: VALVULAR HEART DISEASE and PULMONARY ARTERIAL HYPERTENSION

FINTEPLA can cause valvular heart disease and pulmonary arterial hypertension [see Warnings and Precautions (5.1)].

Echocardiogram assessments are required before, during, and after treatment with FINTEPLA. The benefits versus the risks of initiating or continuing FINTEPLA must be considered, based on echocardiogram findings [see Dosage and Administration (2.1, 2.6) and Warnings and Precautions (5.1)].

Because of the risks of valvular heart disease and pulmonary arterial hypertension, FINTEPLA is available only through a restricted program under a Risk Evaluation and Mitigation Strategy (REMS) called the FINTEPLA REMS [see Warnings and Precautions (5.2)].

1 INDICATIONS AND USAGE

FINTEPLA is indicated for the treatment of seizures associated with Dravet syndrome (DS) and Lennox-Gastaut syndrome (LGS) in patients 2 years of age and older.

2 DOSAGE AND ADMINISTRATION

2.1 Assessments Prior to Initiating FINTEPLA

Prior to starting treatment with FINTEPLA, obtain an echocardiogram assessment to evaluate for valvular heart disease and pulmonary arterial hypertension [see Dosage and Administration (2.6)and Warnings and Precautions (5.1)] .

2.2 Dosing Information

FINTEPLA is to be administered orally and may be taken with or without food.

Dravet Syndrome

- The initial starting and maintenance dosage for patients with Dravet syndrome is 0.1 mg/kg twice daily, which can be increased weekly based on efficacy and tolerability. Table 1 provides the recommended titration schedule, if needed.
- Patients with Dravet syndrome not on concomitant stiripentol who are tolerating FINTEPLA at 0.1 mg/kg twice daily and require further reduction of seizures may benefit from a dosage increase up to a maximum recommended maintenance dosage of 0.35 mg/kg twice daily (maximum daily dosage of 26 mg).
  Patients with Dravet syndrome taking concomitant stiripentol plus clobazam who are tolerating FINTEPLA at 0.1 mg/kg twice daily and require further reduction of seizures may benefit from a dosage increase up to a maximum recommended maintenance dosage of 0.2 mg/kg twice daily (maximum daily dosage of 17 mg) [see Drug Interactions (7.1)].

Lennox-Gastaut Syndrome

- The initial starting dosage for patients with Lennox-Gastaut syndrome is 0.1 mg/kg twice daily, which should be increased weekly based on tolerability. Table 1 provides the recommended titration schedule.
- Patients with Lennox-Gastaut syndrome not on concomitant stiripentol who are tolerating FINTEPLA should be titrated to the recommended maintenance dosage of 0.35 mg/kg twice daily (maximum daily dosage of 26 mg).
- Patients with Lennox-Gastaut syndrome taking concomitant stiripentol plus clobazam who are tolerating FINTEPLA should be titrated to the recommended maintenance dosage of 0.2 mg/kg twice daily (maximum daily dosage of 17 mg) [see Drug Interactions (7.1)].

Table 1: FINTEPLA Recommended Titration Schedule [For patients not on concomitant stiripentol in whom a more rapid titration is warranted, the dose may be increased every 4 days.]
 | Without concomitant stiripentol |  | With concomitant stiripentol plus clobazam
 | Weight-based Dosage [To calculate the dose volume: Weight (kg) × Weight-based dosage (mg/kg) ÷ 2.2 mg/mL = mL dose to be taken twice daily] | Maximum Total Daily Dosage [For maximum dosage with concomitant use of strong CYP1A2 or CYP2D6 inhibitors, in patients with severe renal impairment, or in patients with hepatic impairment see Dosage and Administration 2.3, 2.4, 2.5.] | Weight-based Dosage | Maximum Total Daily Dosage
Initial Dosage [For patients with Dravet syndrome, dosage may be increased based on clinical response to the maximum recommended dosage, as needed.] | 0.1 mg/kg twice daily | 26 mg | 0.1 mg/kg twice daily | 17 mg
Day 7 | 0.2 mg/kg twice daily | 26 mg | 0.15 mg/kg twice daily | 17 mg
Day 14 [For patients with Lennox-Gastaut syndrome, dosage should be increased as tolerated to the recommended maintenance dosage (i.e., Day 14).] | 0.35 mg/kg twice daily | 26 mg | 0.2 mg/kg twice daily | 17 mg

2.3 Dosage Modifications for Patients with Concomitant Use of Strong CYP1A2 or CYP2D6 Inhibitors (DS and LGS)

For patients with concomitant use of FINTEPLA with a strong CYP1A2 or CYP2D6 inhibitor, a maximum total daily dosage of 20 mg without concomitant stiripentol and 17 mg with concomitant stiripentol plus clobazam is recommended [see Drug Interactions (7.1)] .

2.4 Dosage Modifications for Patients with Severe Renal Impairment (DS and LGS)

For patients with severe renal impairment (estimated glomerular filtration rate (eGFR) 15 to 29 mL/min/1.73m^2), a maximum total daily dosage of 20 mg without concomitant stiripentol and 17 mg with concomitant stiripentol plus clobazam is recommended [see Use in Specific Populations (8.6)] .

2.5 Dosage Modifications for Patients with Mild, Moderate, and Severe Hepatic Impairment (DS and LGS)

See Table 2for dosage adjustments and recommendations for patients with hepatic impairment [see Use in Specific Populations (8.7)] .

Table 2: FINTEPLA Dosage Modifications and Recommendations for Patients with Hepatic Impairment
Hepatic Impairment Classification | Without concomitant stiripentol [titrate as recommended [see Dosage and Administration (2.2)]] | With concomitant stiripentol plus clobazam
Hepatic Impairment Classification | Maximum total daily dosage | Maximum total daily dosage
Mild (Child-Pugh A) | 20 mg | 13 mg
Moderate (Child-Pugh B) | 20 mg | Use not recommended
Severe (Child-Pugh C) | 17 mg | Use not recommended

2.6 Assessments During and After Administration of FINTEPLA

To evaluate for valvular heart disease and pulmonary arterial hypertension, obtain an echocardiogram assessment every 6 months during treatment with FINTEPLA, and 3 to 6 months after the final dose of FINTEPLA [see Warnings and Precautions (5.1)].

2.7 Administration Instructions

A calibrated measuring device (either a 3 mL or 6 mL oral syringe) will be provided by the pharmacy and is recommended to measure and administer the prescribed dose accurately [see How Supplied/Storage and Handling (16.1)] . A household teaspoon or tablespoon is not an adequate measuring device and should not be used.

Discard any unused FINTEPLA oral solution remaining after 3 months of first opening the bottle or the "Discard After" date on the bottle, whichever is sooner.

FINTEPLA is compatible with commercially available gastric and nasogastric feeding tubes.

2.8 Discontinuation of FINTEPLA

When discontinuing FINTEPLA, the dose should be decreased gradually. As with all antiepileptic drugs, abrupt discontinuation should be avoided when possible, to minimize the risk of increased seizure frequency and status epilepticus [see Warnings and Precautions (5.6)].

3 DOSAGE FORMS AND STRENGTHS

Oral solution: 2.2 mg/mL fenfluramine as a clear, colorless, cherry flavored liquid.

4 CONTRAINDICATIONS

FINTEPLA is contraindicated in patients with:

- Hypersensitivity to fenfluramine or any of the excipients in FINTEPLA [see Description (11)]
- Concomitant use, or within 14 days of the administration, of monoamine oxidase inhibitors because of an increased risk of serotonin syndrome [see Warnings and Precautions (5.7)]

5 WARNINGS AND PRECAUTIONS

5.1 Valvular Heart Disease and Pulmonary Arterial Hypertension

FINTEPLA can cause valvular heart disease (VHD) and pulmonary arterial hypertension (PAH). There is a known association between serotonergic drugs with 5-HT2B receptor agonist activity, including fenfluramine (the active ingredient in FINTEPLA), and valvular heart disease and pulmonary arterial hypertension. Although no patients receiving FINTEPLA developed valvular heart disease or pulmonary arterial hypertension in clinical trials for DS and LGS of up to 3 years in duration, cases of valvular heart disease and pulmonary arterial hypertension have been reported during use of FINTEPLA in the postmarketing setting [see Boxed Warningand Adverse Reactions (6.1)] .

Because of this risk, cardiac monitoring is required prior to starting treatment, during treatment, and after treatment with FINTEPLA concludes .Cardiac monitoring via echocardiogram can identify evidence of valvular heart disease and pulmonary arterial hypertension prior to a patient becoming symptomatic, aiding in early detection of these conditions.

Monitoring

Prior to starting treatment, patients must undergo an echocardiogram to evaluate for valvular heart disease and pulmonary arterial hypertension.

Echocardiograms should be repeated every 6 months, and once 3-6 months post-treatment with FINTEPLA.

The prescriber must consider the benefits versus the risks of initiating or continuing treatment with FINTEPLA if any of the following signs are observed via ECHO:

- Valvular abnormality or new abnormality via echocardiogram.
- VHD as indicated by mild or greater aortic regurgitation or moderate or greater mitral regurgitation, with additional characteristics of VHD (e.g., valve thickening or restrictive valve motion).
- PAH as indicated by elevated right heart/pulmonary artery pressure (PASP > 35 mm Hg).

FINTEPLA is available only through a restricted program under a REMS [see Warnings and Precautions (5.2)].

5.2 FINTEPLA REMS Program

FINTEPLA is available only through a restricted distribution program called the FINTEPLA REMS program because of the risk of valvular heart disease and pulmonary arterial hypertension [see Warnings and Precautions (5.1)].

Notable requirements of the FINTEPLA REMS Program include:

- Prescribers must be certified by enrolling in the FINTEPLA REMS program.
- Prescribers must counsel patients receiving FINTEPLA about the risk of valvular heart disease and pulmonary arterial hypertension, how to recognize signs and symptoms of valvular heart disease and pulmonary arterial hypertension, the need for baseline (pretreatment) and periodic cardiac monitoring via echocardiogram during FINTEPLA treatment, and cardiac monitoring after FINTEPLA treatment.
- Patients must enroll in the REMS program and comply with ongoing monitoring requirements [see Warnings and Precautions (5.1)].
- The pharmacy must be certified by enrolling in the REMS program and must only dispense to patients who are authorized to receive FINTEPLA.
- Wholesalers and distributors must only distribute to certified pharmacies.

Further information is available at www.FinteplaREMS.com or by telephone at 1-877-964-3649.

5.3 Decreased Appetite and Decreased Weight

FINTEPLA can cause decreases in appetite and weight. In placebo-controlled studies for DS (Study 1 and Study 2 combined), approximately 37% of patients treated with FINTEPLA reported, as an adverse reaction, decreased appetite and approximately 9% reported decreased weight, as compared to 8% and 1%, respectively, of patients on placebo .In the placebo- controlled study for LGS (Study 3), approximately 28% of patients treated with FINTEPLA reported, as an adverse reaction, decreased appetite and approximately 5% reported decreased weight, as compared to 15% and 2%, respectively, of patients on placebo [see Adverse Reactions (6.1)] . By the end of the controlled studies, 19% (Studies 1 and 2 combined) of DS patients and 7% (Study 3) of LGS patients treated with FINTEPLA had a measured decrease in weight of 7% or greater from their baseline weight, compared to 2% (Study 1 and 2) and 0% (Study 3) of patients on placebo. This measured decrease in weight appeared to be dose-related. In the controlled studies for DS, 26% of patients on FINTEPLA 0.7 mg/kg/day (Study 1), 19% of patients on FINTEPLA 0.4 mg/kg/day in combination with stiripentol (Study 2), and 13% of patients taking FINTEPLA 0.2 mg/kg/day (Study 1) experienced at least a 7% decrease in weight from baseline. In the controlled study for LGS, 9% of patients on FINTEPLA 0.7 mg/kg/day (Study 3) and 6% of patients on FINTEPLA 0.2 mg/kg/day (Study 3) experienced at least a 7% decrease in weight from baseline. Approximately half of the patients with LGS and most patients with DS resumed the expected measured increases in weight during the open-label extension studies. Given the frequency of these adverse reactions, the growth of pediatric patients treated with FINTEPLA should be carefully monitored. Weight should be monitored regularly during treatment with FINTEPLA, and dose modifications should be considered if a decrease in weight is observed.

5.4 Somnolence, Sedation, and Lethargy

FINTEPLA can cause somnolence, sedation, and lethargy. In controlled studies for DS (Study 1 and Study 2 combined), the incidence of somnolence, sedation, and lethargy was 25% in patients treated with FINTEPLA, compared with 11% of patients on placebo. In the controlled study for LGS (Study 3), the incidence of somnolence, sedation, and lethargy was 19% in patients treated with FINTEPLA, compared with 16% of patients on placebo. In general, these effects may diminish with continued treatment [see Adverse Reactions (6.1)].

Other central nervous system (CNS) depressants, including alcohol, could potentiate these effects of FINTEPLA. Prescribers should monitor patients for somnolence and sedation and should advise patients not to drive or operate machinery until they have gained sufficient experience on FINTEPLA to gauge whether it adversely affects their ability to drive or operate machinery.

5.5 Suicidal Behavior and Ideation

Antiepileptic drugs (AEDs), including FINTEPLA, increase the risk of suicidal thoughts or behavior in patients taking these drugs for any indication. Patients treated with an AED for any indication should be monitored for the emergence or worsening of depression, suicidal thoughts or behavior, or any unusual changes in mood or behavior.

Pooled analyses of 199 placebo-controlled clinical trials (mono- and adjunctive therapy) of 11 different AEDs that did not include FINTEPLA showed that patients randomized to one of the AEDs had approximately twice the risk (adjusted Relative Risk 1.8, 95% CI:1.2, 2.7) of suicidal thinking or behavior compared to patients randomized to placebo. In these trials, which had a median treatment duration of 12 weeks, the estimated incidence rate of suicidal behavior or ideation among 27,863 AED-treated patients was 0.43%, compared to 0.24% among 16,029 placebo-treated patients, representing an increase of approximately one case of suicidal thinking or behavior for every 530 patients treated. There were four suicides in drug-treated patients in the trials and none in placebo-treated patients, but the number is too small to allow any conclusion about drug effect on suicide.

The increased risk of suicidal thoughts or behavior with AEDs was observed as early as 1 week after starting drug treatment with AEDs and persisted for the duration of treatment assessed. Because most trials included in the analysis did not extend beyond 24 weeks, the risk of suicidal thoughts or behavior beyond 24 weeks could not be assessed.

The risk of suicidal thoughts or behavior was generally consistent among drugs in the data analyzed. The finding of increased risk with AEDs of varying mechanisms of action and across a range of indications suggests that the risk applies to all AEDs used for any indication. The risk did not vary substantially by age (5-100 years) in the clinical trials analyzed. Table 3 shows absolute and relative risk by indication for all evaluated AEDs.

Table 3: Risk of Suicidal Thoughts or Behaviors by Indication for Antiepileptic Drugs in the Pooled Analysis
Indication | Placebo Patients with Events per 1000 Patients | Drug Patients with Events per 1000 Patients | Relative Risk: Incidence of Events in Drug Patients/ Incidence in Placebo Patients | Risk Difference: Additional Drug Patients with Events per 1000 Patients
Epilepsy | 1.0 | 3.4 | 3.5 | 2.4
Psychiatric | 5.7 | 8.5 | 1.5 | 2.9
Other | 1.0 | 1.8 | 1.9 | 0.9
Total | 2.4 | 4.3 | 1.8 | 1.9

The relative risk for suicidal thoughts or behavior was higher in clinical trials in patients with epilepsy than in clinical trials in patients with psychiatric or other conditions, but the absolute risk differences were similar for the epilepsy and psychiatric indications.

Anyone considering prescribing FINTEPLA or any other AED must balance the risk of suicidal thoughts or behaviors with the risk of untreated illness. Epilepsy and many other illnesses for which AEDs are prescribed are themselves associated with morbidity and mortality and an increased risk of suicidal thoughts and behavior. Should suicidal thoughts and behavior emerge during treatment, consider whether the emergence of these symptoms in any given patient may be related to the illness being treated.

5.6 Withdrawal of Antiepileptic Drugs

As with most AEDs, FINTEPLA should generally be withdrawn gradually because of the risk of increased seizure frequency and status epilepticus. If withdrawal is needed because of a serious adverse reaction, rapid discontinuation can be considered.

5.7 Serotonin Syndrome

Serotonin syndrome, a potentially life-threatening condition, may occur with FINTEPLA, particularly with concomitant administration of FINTEPLA with other serotonergic drugs, including, but not limited to, selective serotonin-norepinephrine reuptake inhibitors (SNRIs), selective serotonin reuptake inhibitors (SSRIs), tricyclic antidepressants (TCAs), bupropion, triptans, dietary supplements (e.g., St. John's Wort, tryptophan), drugs that impair metabolism of serotonin (including monoamine oxidase inhibitors [MAOIs], which are contraindicated with FINTEPLA [see Contraindications (4)], dextromethorphan, lithium, tramadol, and antipsychotics with serotonergic agonist activity. Patients should be monitored for the emergence of signs and symptoms of serotonin syndrome, which include mental status changes (e.g., agitation, hallucinations, coma), autonomic instability (e.g., tachycardia, labile blood pressure, hyperthermia), neuromuscular signs (e.g., hyperreflexia, incoordination), and/or gastrointestinal symptoms (e.g., nausea, vomiting, diarrhea). If serotonin syndrome is suspected, treatment with FINTEPLA should be stopped immediately and symptomatic treatment should be started.

5.8 Increase in Blood Pressure

FINTEPLA can cause an increase in blood pressure [see Adverse Reactions (6.1)]. Rare cases of significant elevation in blood pressure, including hypertensive crisis, has been reported in adult patients treated with fenfluramine, including patients without a history of hypertension. In clinical trials of up to 3 years in duration, no pediatric or adult patient receiving FINTEPLA developed a hypertensive crisis. Monitor blood pressure in patients treated with FINTEPLA.

5.9 Glaucoma

Fenfluramine can cause mydriasis and can precipitate angle closure glaucoma. Consider discontinuing treatment with FINTEPLA in patients with acute decreases in visual acuity or ocular pain.

6 ADVERSE REACTIONS

The following clinically significant adverse reactions are described elsewhere in labeling:

- Valvular Heart Disease and Pulmonary Arterial Hypertension [see Warnings and Precautions (5.1)]
- Decreased Appetite and Decreased Weight [see Warnings and Precautions (5.3)]
- Somnolence, Sedation, and Lethargy [see Warnings and Precautions (5.4)]
- Suicidal Behavior and Ideation [see Warnings and Precautions (5.5)]
- Withdrawal of Antiepileptic Drugs [see Warnings and Precautions (5.6)]
- Serotonin Syndrome [see Warnings and Precautions (5.7)]
- Increase in Blood Pressure [see Warnings and Precautions (5.8)]
- Glaucoma [see Warnings and Precautions (5.9)]

6.1 Clinical Trials Experience

Because clinical trials are conducted under widely varying conditions, adverse reaction rates observed in the clinical trials of a drug cannot be directly compared to rates in the clinical trials of another drug and may not reflect the rates observed in practice.

In controlled and uncontrolled trials in patients with Dravet syndrome (DS), 341 patients were treated with FINTEPLA, including 312 patients treated for more than 6 months, 284 patients treated for more than 1 year, and 138 patients treated for more than 2 years.

In controlled and uncontrolled trials in patients with Lennox-Gastaut syndrome (LGS), 262 patients were treated with FINTEPLA, including 219 patients treated for more than 6 months, 172 patients treated for more than 1 year, and 127 patients treated for more than 2 years.

Dravet Syndrome

In placebo-controlled trials of patients with DS taking concomitant standard of care AEDs, 122 patients were treated with FINTEPLA and 84 patients received placebo [see Clinical Studies (14.1)] . The duration of treatment in these trials was 16 weeks (Study 1) or 17 weeks (Study 2).

In Study 1 and Study 2, the mean age was 9 years (range 2 to 19 years) and approximately 46% of patients were female and 74% were White. All patients were receiving at least one other AED.

In Study 1 and Study 2, the rates of discontinuation as a result of any adverse reaction were 13%, 0%, and 7% for patients treated with FINTEPLA 0.7 mg/kg/day, 0.2 mg/kg/day, and 0.4 mg/kg/day in combination with stiripentol, respectively, compared to 6% for patients on placebo. The most frequent adverse reaction leading to discontinuation in the patients treated with any dose of FINTEPLA was somnolence (3%).

The most common adverse reactions that occurred in patients treated with FINTEPLA (incidence at least 10% and greater than placebo) were decreased appetite; somnolence, sedation, lethargy; diarrhea; constipation; abnormal echocardiogram; fatigue, malaise, asthenia; ataxia, balance disorder, gait disturbance; blood pressure increased; drooling, salivary hypersecretion; pyrexia; upper respiratory tract infection; vomiting; decreased weight; fall; status epilepticus.

Table 4 lists the adverse reactions that were reported in 5% or more of patients treated with FINTEPLA and at a rate greater than those on placebo during the titration and maintenance phases of Study 1 and Study 2.

Table 4: Adverse Reactions in 5% or More of Patients Treated with FINTEPLA and Greater Than Placebo in Placebo-Controlled Trials for Dravet Syndrome (Study 1 and 2)
Adverse Reaction | FINTEPLA Dose Group |  |  | Combined Placebo Group [Patients in placebo groups from Studies 1 and 2 were pooled.]
Adverse Reaction | Study 1 |  | Study 2 | Combined Placebo Group [Patients in placebo groups from Studies 1 and 2 were pooled.]
Adverse Reaction | 0.2 mg/kg/day | 0.7 mg/kg/day | 0.4 mg/kg/day [0.4 mg/kg/day was not an intermediate dose. Patients on the 0.4 mg/kg/day dose were also taking concomitant stiripentol plus clobazam, which increases exposure of FINTEPLA.] | Combined Placebo Group [Patients in placebo groups from Studies 1 and 2 were pooled.]
Adverse Reaction | N=39 % | N=40 % | N=43 % | N=84 %
Decreased appetite | 23 | 38 | 49 | 8
Somnolence, sedation, lethargy | 26 | 25 | 23 | 11
Abnormal echocardiogram [Consisted of trace and mild mitral regurgitation, and trace aortic regurgitation, which are considered physiologic.] | 18 | 23 | 9 | 6
Diarrhea | 31 | 15 | 23 | 6
Constipation | 3 | 10 | 7 | 0
Fatigue, malaise, asthenia | 15 | 10 | 30 | 5
Ataxia, balance disorder, gait disturbance | 10 | 10 | 7 | 1
Abnormal behavior | 0 | 8 | 9 | 0
Blood pressure increased | 13 | 8 | 0 | 5
Drooling, salivary hypersecretion | 13 | 8 | 2 | 0
Hypotonia | 0 | 8 | 0 | 0
Rash | 8 | 8 | 5 | 4
Blood prolactin increased | 0 | 5 | 0 | 0
Chills | 0 | 5 | 2 | 0
Decreased activity | 0 | 5 | 0 | 1
Dehydration | 0 | 5 | 0 | 0
Insomnia | 0 | 5 | 5 | 2
Pyrexia | 15 | 5 | 21 | 14
Stereotypy | 0 | 5 | 0 | 0
Upper respiratory tract infection | 21 | 5 | 7 | 10
Vomiting | 10 | 5 | 5 | 8
Weight decreased | 13 | 5 | 7 | 1
Croup | 5 | 3 | 0 | 1
Ear infection | 8 | 3 | 9 | 5
Gastroenteritis | 8 | 3 | 2 | 0
Increased heart rate | 5 | 3 | 0 | 2
Irritability | 0 | 3 | 9 | 2
Rhinitis | 8 | 3 | 7 | 2
Tremor | 3 | 3 | 9 | 0
Urinary incontinence | 5 | 3 | 0 | 0
Decreased blood glucose | 0 | 0 | 9 | 1
Bronchitis | 3 | 0 | 9 | 1
Contusion | 5 | 0 | 0 | 0
Eczema | 0 | 0 | 5 | 0
Enuresis | 5 | 0 | 0 | 0
Fall | 10 | 0 | 0 | 4
Headache | 8 | 0 | 0 | 2
Laryngitis | 0 | 0 | 5 | 0
Negativism | 5 | 0 | 0 | 0
Status epilepticus | 3 | 0 | 12 | 2
Urinary tract infection | 5 | 0 | 5 | 0
Viral infection | 0 | 0 | 5 | 1

Lennox-Gastaut Syndrome

In the placebo-controlled trial of patients with LGS taking concomitant standard of care AEDs (Study 3), 176 patients were treated with FINTEPLA and 87 patients received placebo [see Clinical Studies (14.2)] . The duration of treatment in this trial was 16 weeks. The mean age was 13.7 years (range 2 to 35 years) and 29% of patients were at least 18 years of age, 45% of patients were female, and 79% were White. All patients were receiving at least one other AED.

The rates of discontinuation as a result of any adverse reaction were 6% and 5% for patients treated with FINTEPLA 0.7 mg/kg/day and 0.2 mg/kg/day, respectively, compared to 1% for patients on placebo. The most frequent adverse reactions leading to discontinuation in the patients treated with any dose of FINTEPLA were seizure (2%) and somnolence (2%).

The common adverse reactions that occurred in patients treated with FINTEPLA (incidence at least 10% and greater than placebo) were diarrhea; decreased appetite; fatigue; somnolence; vomiting.

Table 5 lists the adverse reactions that were reported in 5% or more of patients treated with FINTEPLA and at a rate greater than those on placebo during the titration and maintenance phases of Study 3.

Table 5: Adverse Reactions in 5% or More of Patients Treated with FINTEPLA and Greater Than Placebo in the Placebo-Controlled Trial for Lennox Gastaut Syndrome (Study 3)
Adverse Reaction | FINTEPLA Dose Group
Adverse Reaction | Study 3 |  | Placebo Group
Adverse Reaction | 0.2 mg/kg/day | 0.7mg/kg/day | Placebo Group
Adverse Reaction | N=89 % | N=87 % | N=87 %
Decreased appetite | 20 | 36 | 12
Fatigue, malaise, asthenia | 14 | 24 | 16
Somnolence, sedation, lethargy | 12 | 22 | 16
Diarrhea | 11 | 13 | 5
Constipation | 6 | 9 | 6
Vomiting | 14 | 8 | 6
Weight decreased | 2 | 8 | 2
Upper respiratory tract infection | 8 | 7 | 3
Seizure | 9 | 5 | 7
Irritability | 8 | 3 | 6

Echocardiographic Safety Assessments of Valvular Heart Disease and Pulmonary Arterial Hypertension

Valvular heart disease and pulmonary arterial hypertension were evaluated in the placebo- controlled and open-label extension studies via echocardiography for up to 3 years in duration for 341 DS patients and 263 LGS patients [see Warnings and Precautions (5.1)]. Screening for valvular heart disease assessed for mild or greater aortic regurgitation or moderate or greater mitral regurgitation, and assessed for additional characteristics of VHD (e.g., valve thickening or restrictive valve motion).

In these clinical studies, two patients with LGS exhibited mild aortic regurgitation (AR) but neither patient had any cardiac signs or symptoms or evidence of valvular structural changes. Neither patient had VHD. The rates of mild AR are consistent with those seen in the screening period prior to treatment (3 patients in LGS and 1 patient in DS clinical trials).

6.2 Postmarketing Experience

The following adverse reactions have been identified during postapproval use of FINTEPLA. Because these reactions are reported voluntarily from a population of uncertain size, it is not always possible to reliably estimate their frequency or establish a causal relationship to drug exposure.

Psychiatric disorders: aggression

7 DRUG INTERACTIONS

7.1 Effect of Other Drugs on FINTEPLA

Stiripentol Plus Clobazam

Coadministration of FINTEPLA with stiripentol plus clobazam, with or without valproate, increases fenfluramine plasma concentrations [see Clinical Pharmacology (12.3)]. If FINTEPLA is coadministered with stiripentol plus clobazam, the maximum daily dosage of FINTEPLA is 0.2 mg/kg twice daily (maximum daily dosage of 17 mg) [see Dosage and Administration (2.2)] .

Strong CYP1A2, CYP2B6, or CYP3A Inducers

Coadministration of FINTEPLA with strong CYP1A2, CYP2B6, or CYP3A inducers will decrease fenfluramine plasma concentrations, which may lower the efficacy of FINTEPLA [see Clinical Pharmacology (12.3)] .

It is recommended to avoid coadministration of strong CYP1A2, CYP2B6 or CYP3A inducers. If coadministration of a strong CYP1A2, CYP2B6, or CYP3A inducer with FINTEPLA is necessary, monitor the patient for reduced efficacy and consider increasing the dosage of FINTEPLA as needed; however, do not exceed the maximum daily dosage of FINTEPLA [see Dosage and Administration (2.2)].

If a strong CYP1A2, CYP2B6, or CYP3A inducer is discontinued during maintenance treatment with FINTEPLA, consider gradual reduction in the FINTEPLA dosage to the dose administered prior to initiating the inducer [see Warnings and Precautions (5.6)].

Strong CYP1A2 or CYP2D6 Inhibitors

Coadministration of FINTEPLA with strong CYP1A2 or CYP2D6 inhibitors will increase fenfluramine plasma concentrations [see Clinical Pharmacology (12.3)] . If FINTEPLA is coadministered with strong CYP1A2 or CYP2D6 inhibitors, the maximum daily dosage of FINTEPLA is 20 mg [see Dosage and Administration (2.3)].

If a strong CYP1A2 or CYP2D6 inhibitor is discontinued during maintenance treatment with FINTEPLA, consider gradual increase in the FINTEPLA dosage to the dose recommended without CYP1A2 or CYP2D6 inhibitors; however, do not exceed the maximum daily dosage of FINTEPLA [see Dosage and Administration (2.2)].

If FINTEPLA is coadministered with stiripentol and a strong CYP1A2 or CYP2D6 inhibitor, do not exceed the maximum daily dosage of FINTEPLA of 17 mg [see Dosage and Administration (2.3)].

7.2 Effects of Serotonin Receptor Antagonists

Cyproheptadine and potent 5-HT1A, 5-HT1D, 5-HT2A, and 5-HT2C serotonin receptor antagonists may decrease the efficacy of FINTEPLA. If cyproheptadine or potent 5--HT1A, 5--HT1D, 5-HT2A, or 5-HT2C serotonin receptor antagonists are coadministered with FINTEPLA, patients should be monitored appropriately.

7.3 Serotonergic Drugs

Concomitant administration of FINTEPLA and drugs (e.g., SSRIs, SNRIs, TCAs, MAO inhibitors, trazodone, etc.), over-the-counter medications (e.g., dextromethorphan), or herbal supplements (e.g., St. John's Wort) that increase serotonin may increase the risk of serotonin syndrome [see Warnings and Precautions (5.7)]. Concomitant use of FINTEPLA is contraindicated within 14 days of taking MAOIs. Use FINTEPLA with caution in patients taking other medications that increase serotonin.

8 USE IN SPECIFIC POPULATIONS

8.1 Pregnancy

Pregnancy Exposure Registry

There is a pregnancy exposure registry that monitors pregnancy outcomes in women exposed to antiepileptic drugs (AEDs), such as FINTEPLA, during pregnancy. Encourage women who are taking FINTEPLA during pregnancy to enroll in the North American Antiepileptic Drug (NAAED) Pregnancy Registry by calling the toll-free number 1-888-233-2334 or visiting http://www.aedpregnancyregistry.org.

Risk Summary

There are no data on FINTEPLA use in pregnant women. Available data from epidemiologic studies with fenfluramine or dexfenfluramine are insufficient to evaluate for a drug-associated risk of major birth defects, miscarriage, or other adverse maternal or fetal outcomes. FINTEPLA can cause decreased appetite and decreased weight [see Warnings and Precautions (5.3)]; monitor for adequate weight gain during pregnancy. In animal studies, administration of fenfluramine throughout organogenesis (rat and rabbit) or throughout gestation and lactation (rat) resulted in adverse effects on development (fetal malformations, embryofetal and offspring mortality and growth impairment) in the presence of maternal toxicity at clinically relevant maternal plasma levels of fenfluramine and its major active metabolite (see Data) .

All pregnancies have a background risk of birth defect, loss, or other adverse outcomes. In the U.S. general population, the estimated background risk of major birth defects and miscarriage in clinically recognized pregnancies is 2 to 4% and 15 to 20%, respectively.

Clinical Considerations

Disease-associated Maternal and/or Embryofetal Risk

Epilepsy, with or without exposure to antiepileptic drugs, has been associated with several adverse outcomes during pregnancy, including preeclampsia, preterm labor, antepartum and postpartum hemorrhage, placental abruption, poor fetal growth, prematurity, fetal death, and maternal mortality. The risk of maternal or fetal injury may be greatest for patients with untreated or poorly controlled convulsive seizures. Women with epilepsy who become pregnant should not abruptly discontinue antiepileptic drugs, including FINTEPLA, due to the risk of status epilepticus or severe seizures, which may be life-threatening [see Warnings and Precautions (5.6)].

Data

Animal Data

Oral administration of fenfluramine (0, 4.5, 8.6, or 34.6 mg/kg/day) to pregnant rats during organogenesis resulted in decreased fetal body weights and marked increases in fetal malformations (external, visceral, and skeletal) at the highest dose tested, which was associated with maternal toxicity. At the no-effect dose (8.6 mg/kg/day) for adverse effects on embryofetal development in rats, maternal plasma exposures (AUC) of fenfluramine and norfenfluramine (the major metabolite) were approximately 2 and 5 times, respectively, those in humans at the maximum recommended human dose (MRHD) of 26 mg/day.

Oral administration of fenfluramine (0, 4.3, 8.6, 13.0 mg/kg/day) to pregnant rabbits throughout organogenesis resulted in increased embryofetal mortality at all doses and increases in fetal malformations (external and skeletal) at the highest dose tested, which was associated with maternal toxicity. A no-adverse-effect dose for adverse effects on embryofetal development in rabbits was not identified. At the lowest dose tested in rabbits (4.3 mg/kg/day), maternal plasma exposures of fenfluramine and norfenfluramine were lower than those in humans at the MRHD.

Oral administration of fenfluramine (0, 4.3, 8.6, or 34.6 mg/kg/day) to female rats throughout gestation and lactation resulted in marked increases in stillborn pups and neonatal offspring deaths at the highest dose tested and delayed growth and reflex development during the pre- weaning period at all doses. Maternal body weight gain was decreased at all doses during pregnancy and at the two highest doses during lactation. A no-effect dose for adverse effects on pre- and postnatal development in rats was not determined. At the lowest dose tested in rats (4.3 mg/kg/day), maternal plasma exposures of fenfluramine and norfenfluramine were approximately 0.5 and 3 times, respectively, those in humans at the MRHD.

8.2 Lactation

Risk Summary

There are no data on the presence of fenfluramine or its metabolites in human milk, the effects on the breastfed infant, or the effects on milk production.

The developmental and health benefits of breastfeeding should be considered along with the mother's clinical need for FINTEPLA and any potential adverse effects on the breastfed infant from FINTEPLA or from the underlying maternal condition.

8.3 Females and Males of Reproductive Potential

Infertility

In animal studies, oral administration of fenfluramine resulted in adverse reproductive effects in males and females at clinically relevant doses in the presence of parental toxicity [see Nonclinical Toxicology (13.1)] .

8.4 Pediatric Use

The safety and effectiveness of FINTEPLA for the treatment of seizures associated with DS and LGS have been established in patients 2 years of age and older.

Use of FINTEPLA for the treatment of seizures associated with DS in patients 2 years of age and older is supported by two randomized, double-blind, placebo-controlled trials in 202 patients 2 to 18 years of age. Use of FINTEPLA for the treatment of seizures associated with LGS is supported by a randomized, double-blind, placebo-controlled study in 263 patients aged 2 to 35 years, including 187 patients less than 18 years [see Boxed Warning, Warnings and Precautions (5), Adverse Reaction (6.1), and Clinical Studies (14)].

FINTEPLA can cause decreases in appetite and weight. The growth of pediatric patients treated with FINTEPLA should be carefully monitored.

Safety and effectiveness in patients less than 2 years of age have not been established.

Juvenile Animal Data

Oral administration of fenfluramine (0, 3.0, 7.8, or 17.3 mg/kg/day) to young rats for 10 weeks starting on postnatal day 7 resulted in reduced body weight and neurobehavioral changes (decreased locomotor activity and learning and memory deficits) at all doses tested. Neurobehavioral effects persisted after dosing was discontinued. Bone size was decreased at the mid and high doses; brain size was decreased at the highest dose. Partial or complete recovery was seen for these endpoints. A no-effect dose for postnatal developmental toxicity was not identified. The lowest dose tested (3.0 mg/kg/day) was associated with plasma fenfluramine exposures (AUC) less than that in humans at the maximum recommended human dose (MRHD) of 26 mg/day and norfenfluramine (metabolite) exposures (AUC) approximately 2 times that in humans at the MRHD.

8.5 Geriatric Use

Clinical studies of FINTEPLA for the treatment of DS or LGS did not include patients 65 years of age and over to determine whether they respond differently from younger patients. In general, dose selection for an elderly patient should be cautious, usually starting at the low end of the dosing range, reflecting the greater frequency of decreased hepatic, renal, or cardiac function, and of concomitant disease or other drug therapy.

8.6 Renal Impairment

In patients with estimated glomerular filtration rate (eGFR) 15 to 29 mL/min/1.73m^2, do not exceed the maximum daily dosage of FINTEPLA of 20 mg .In patients with eGFR 15 to 29 ml/min/1.73m^2and concomitant stiripentol use, do not exceed the maximum daily dosage of FINTEPLA of 17 mg [see Dosage and Administration (2.4)and Clinical Pharmacology (12.3)]. FINTEPLA has not been studied in patients with eGFR < 15 mL/min/1.73m^2.

8.7 Hepatic Impairment

Combined molar exposures of fenfluramine and norfenfluramine were increased in subjects with various degrees of hepatic impairment (Child-Pugh Class A, B, and C), necessitating a dosage adjustment in these patients [see Dosage and Administration (2.5)and Clinical Pharmacology (12.3)] .

10 OVERDOSAGE

Overdose has not been observed in the FINTEPLA clinical trial program. However, overdose of fenfluramine, the active ingredient in FINTEPLA, has been reported at higher doses than those included in the clinical trial program. Some of the cases were fatal. Events reported after overdose include mydriasis, tachycardia, flushing, tremors/twitching/muscle spasms, agitation/restlessness/anxiety, increased muscle tone/rigor/opisthotonos, respiratory distress or failure, and seizure. Seizure, coma, and cardiorespiratory arrest were reported in most of the fatal overdoses.

There is no available specific antidote to the overdose reactions of FINTEPLA. In the event of overdose, standard medical practice for the management of drug overdosage should be used. An adequate airway, oxygenation, and ventilation should be ensured; monitoring of cardiac rhythm and vital sign measurement is recommended. A certified poison control center should be contacted for updated information on the management of overdose with FINTEPLA.

11 DESCRIPTION

FINTEPLA oral solution contains 2.2 mg/mL fenfluramine, equivalent to 2.5 mg/mL of the hydrochloride salt.

The active ingredient, fenfluramine hydrochloride, is designated chemically as N-ethyl-α- methyl-3-(trifluoromethyl)phenethylamine hydrochloride.

The structural formula is:

Fenfluramine hydrochloride is a white to off-white crystalline solid. The pKa of fenfluramine is 10.2.

FINTEPLA is a clear, colorless solution, pH 5.

FINTEPLA contains the following inactive ingredients: cherry flavor, citric acid, ethylparaben hydroxyethylcellulose, methylparaben, potassium citrate, sucralose, and water.

FINTEPLA contains no ingredient made from gluten-containing grain (wheat, barley, or rye), and contains not more than 0.1% of carbohydrates, which is solely derived from the cherry flavor.

12 CLINICAL PHARMACOLOGY

12.1 Mechanism of Action

The precise mechanism by which fenfluramine exerts its therapeutic effects in the treatment of seizures associated with Dravet syndrome and Lennox-Gastaut syndrome is unknown. Fenfluramine and the metabolite, norfenfluramine, exhibit agonist activity at serotonin 5-HT2 receptors. There is an association between serotonergic drugs with 5-HT2B receptor agonist activity, including fenfluramine and norfenfluramine, and valvular heart disease and pulmonary arterial hypertension.

12.2 Pharmacodynamics

Cardiac Electrophysiology

At a dose 4 times the maximum recommended dose, FINTEPLA did not prolong the QT interval when tested in an adult population.

12.3 Pharmacokinetics

The pharmacokinetics of fenfluramine and norfenfluramine were studied in healthy subjects, in pediatric patients with DS, and in pediatric and adult patients with LGS. The steady-state systemic exposure (Cmaxand AUC) of fenfluramine was slightly greater than dose proportional over the dose range of 13 to 51.8 mg twice-daily fenfluramine (i.e., 1 to 4 times the maximum recommended dose). In pediatric patients with DS who received FINTEPLA 0.7 mg/kg/day, up to a total daily dose of 26 mg fenfluramine, the geometric mean steady-state fenfluramine (coefficient of variation) Cmaxwas 68.0 (41%) ng/mL and AUC0-24hwas 1390 (44%) ng*h/mL.

Absorption

Fenfluramine has a time to maximum plasma concentration (Tmax) of 3 to 5 hours at steady state. The absolute bioavailability of fenfluramine is approximately 68-74%. There was no effect of food on the pharmacokinetics of fenfluramine or norfenfluramine.

Distribution

The geometric mean (CV%) apparent volume of distribution (Vz/F) of fenfluramine is 11.9 (16.5%) L/kg following oral administration of FINTEPLA in healthy subjects. Fenfluramine is 50% bound to human plasma proteins in vitro and binding is independent of drug concentrations.

Elimination

The elimination half-life of fenfluramine was 20 hours and the geometric mean (CV%) clearance (CL/F) was 24.8 (29%) L/h, following oral administration of FINTEPLA in healthy subjects.

Metabolism

Over 75% of fenfluramine is metabolized to norfenfluramine prior to elimination, primarily by CYP1A2, CYP2B6, and CYP2D6. Other CYP enzymes involved to a minor extent are CYP2C9, CYP2C19, and CYP3A4/5. Both fenfluramine and norfenfluramine are pharmacologically active. Norfenfluramine is further deaminated and oxidized to form inactive metabolites.

Excretion

Most of an orally administered dose of fenfluramine (greater than 90%) is excreted in the urine as fenfluramine, norfenfluramine, or other metabolites with fenfluramine and norfenfluramine accounting for less than 25% of the total; less than 5% is found in feces.

Specific Populations

The effect of age (range: 2 to 50 years), sex, and race had no clinically meaningful effect on the pharmacokinetics of fenfluramine.

Patients with Renal Impairment

In a dedicated clinical study comparing the pharmacokinetics of a single dose of 0.35 mg/kg FINTEPLA in subjects with severe renal impairment (eGFR < 30 mL/min/1.73m^2determined by MDRD) and matched healthy volunteers, Cmaxand AUC0-infof fenfluramine increased by 20% and 88%, respectively, and Cmaxand AUC0-infof norfenfluramine increased by 13% and 21%, respectively in subjects with severe renal impairment [see Use in Specific Populations (8.6)] . FINTEPLA has not been studied in patients with eGFR < 15 mL/min/1.73m^2(determined by MDRD). It is not known if fenfluramine or norfenfluramine is dialyzable.

Patients with Hepatic Impairment

In a study comparing the pharmacokinetics of a single dose of 0.35 mg/kg FINTEPLA in subjects with mild, moderate, or severe hepatic impairment (Child-Pugh Class A, B, or C) and subjects with normal liver function, AUC0-tof fenfluramine increased by 95%, 113%, and 185% in subjects with mild, moderate, and severe hepatic impairment, respectively. Cmaxof fenfluramine increased by 19%, 16%, and 29% in subjects with mild, moderate, and severe hepatic impairment, respectively. AUC0-tof norfenfluramine increased by 18% in mild hepatic impairment, 4% in moderate hepatic impairment, and decreased by 11% in severe hepatic impairment. Cmaxof norfenfluramine decreased by 21%, 36%, and 45% in subjects with mild, moderate, and severe hepatic impairment, respectively. Combined molar AUC0-tof fenfluramine and norfenfluramine increased by 55%, 56%, and 82% in subjects with mild, moderate, and severe hepatic impairment, respectively. Combined molar Cmaxof fenfluramine and norfenfluramine increased by 7.5%, 1.3%, and 8% in subjects with mild, moderate, and severe hepatic impairment, respectively. The maximum daily dosage of FINTEPLA should be reduced in patients with mild hepatic impairment with/without stiripentol plus clobazam. The maximum daily dosage of FINTEPLA should be reduced in patients with moderate or severe hepatic impairment without stiripentol plus clobazam [see Dosage and Administration (2.5)and Use in Specific Populations (8.7)].

Drug Interaction Studies

Clinical Studies

Effect of a single dose of stiripentol, clobazam, and valproic acid combination:

Coadministration of a single 0.7 mg/kg dose of FINTEPLA, with a single dose of a stiripentol, clobazam, and valproic acid combination in healthy volunteers, increased the AUC0-infof fenfluramine by 69% and the Cmaxby 18%, and decreased the AUC0-72hours of norfenfluramine by 41% and the Cmaxby 42%, as compared to FINTEPLA administered alone.

Effect of steady state stiripentol plus clobazam, with or without valproate:

Fenfluramine pharmacokinetic data were collected from patients after receiving multiple fenfluramine administrations in Study 1 as well as Study 2. Population pharmacokinetic modeling and simulation were used to assess the effect of stiripentol plus clobazam with or without valproate on fenfluramine pharmacokinetics. The effect of stiripentol plus clobazam, with or without valproate, on fenfluramine pharmacokinetics is greater when FINTEPLA is at steady-state than for the first dose of FINTEPLA. At steady state in the patient population, the coadministration of 0.1 mg/kg twice daily (0.2 mg/kg/day), maximum 17 mg/day, of FINTEPLA with stiripentol plus clobazam with or without valproate, is expected to result in a 166% increase in fenfluramine AUC0-24and a 38% decrease in norfenfluramine AUC0-24, as compared to 0.2 mg/kg/day, maximum 26 mg/day, FINTEPLA dose administered alone [see Dosage and Administration (2.1, 2.2)and Drug Interactions (7.1)] .

Effect of steady state cannabidiol:

Coadministration of a single 0.35 mg/kg dose of FINTEPLA with repeated doses of cannabidiol increased the AUC0-infof fenfluramine by 59% and the Cmaxby 10%, and decreased the AUC0-infof norfenfluramine by 22% and the Cmaxby 33%, as compared to FINTEPLA administered alone. This interaction is not expected to be clinically significant.

Effect of strong CYP1A2 or CYP2D6 inhibitors:

Coadministration of a single 0.35 mg/kg dose of FINTEPLA with fluvoxamine (a strong CYP1A2 inhibitor) at steady state (50 mg once daily) in healthy volunteers increased the AUC0- infof fenfluramine by 102% and the Cmaxby 22%, and decreased the AUC0-infof norfenfluramine by 22% and the Cmaxby 44%, as compared to FINTEPLA administered alone [see Drug Interactions (7.1)].

Coadministration of a single 0.35 mg/kg dose of FINTEPLA with paroxetine (a strong CYP2D6 inhibitor) at steady state (30 mg once daily) in healthy volunteers increased the AUC0-infof fenfluramine by 81% and the Cmaxby 13%, and decreased the AUC0-infof norfenfluramine by 13% and the Cmaxby 29%, as compared to FINTEPLA administered alone [see Drug Interactions (7.1)].

Effect of strong CYP1A2, CYP2B6 or CYP3A inducers:

Coadministration of a single 0.35 mg/kg dose of FINTEPLA with rifampin (a CYP1A2, CYP2B6, and CYP3A inducer) at steady state (600 mg once daily) in healthy volunteers decreased the AUC0-infof fenfluramine by 58% and the Cmaxby 40%, and decreased the AUC0-infof norfenfluramine by 50%, and increased the Cmaxof norfenfluramine by 13%, as compared to FINTEPLA administered alone [see Drug Interactions (7.1)].

Effect of FINTEPLA on other drugs:

Coadministration of a single 0.7 mg/kg dose of FINTEPLA, with a single dose of a stiripentol, clobazam, and valproic acid combination, did not affect the pharmacokinetics of stiripentol, nor the pharmacokinetics of clobazam or its N‑desmethyl-metabolite norclobazam, nor the pharmacokinetics of valproic acid, as compared to the stiripentol, clobazam, and valproic acid combination alone. Coadministration of a single 0.35 mg/kg dose of FINTEPLA, with repeated doses of cannabidiol, did not affect the pharmacokinetics of cannabidiol, as compared to cannabidiol alone.

In Vitro Studies

Fenfluramine is primarily metabolized by CYP1A2, CYP2B6, and CYP2D6 in vitro. Other CYP enzymes involved to a minor extent are CYP2C9, CYP2C19, and CYP3A4/5.

Effect of fenfluramine and norfenfluramine on CYP Substrates: fenfluramine and norfenfluramine are not inhibitors or inducers of CYP1A2, CYP2B6, CYP2C8, CYP2C9, CYP2C19, CYP2D6, or CYP3A4 at clinically relevant concentrations.

Effect of transporters on fenfluramine and norfenfluramine: fenfluramine and norfenfluramine are not substrates of the P-g, BCRP, OAT1, OAT3, OCT2, MATE1, or MATE2-K transporters.

Effect of FINTEPLA on Transporters: fenfluramine and norfenfluramine are not inhibitors of P-gp, BCRP, OAT1B1, OATP1B3, OAT1, OAT3, OCT2, MATE1, or MATE2-K transporters.

13 NONCLINICAL TOXICOLOGY

13.1 Carcinogenesis, Mutagenesis, Impairment of Fertility

Carcinogenesis

Oral administration of fenfluramine to Tg.rasH2 mice (0, 4.3, 13.0, 34.6, or 51.8 mg/kg/day) for 26 weeks and to male and female rats (0, 0.9, 2.2, or 6.9 mg/kg/day) for 89 and 97 weeks, respectively, resulted in no evidence of drug-induced tumors in either species. In rats, plasma exposures (AUC) of fenfluramine and norfenfluramine (the major metabolite) at the highest dose tested were approximately 5 and 11 times, respectively, those in humans at the maximum recommended human dose (MRHD) of 26 mg/day.

Mutagenesis

Fenfluramine was negative in an in vitro bacterial mutation (Ames) assay and an in vivo micronucleus and comet assay in rats.

Impairment of Fertility

Oral administration of fenfluramine (0, 3.0, 6.9, or 17.3 mg/kg/day) to male and female rats prior to and throughout mating and continuing in females to day 7 of gestation resulted in a decrease in fertility and increases in abnormal sperm and epithelial vacuolation of the epididymis at the highest dose tested and altered estrous cyclicity, decreased corpora lutea and implantations, and increased embryolethality at the mid and high dose. These doses were associated with parental toxicity. The no-effect doses for adverse effects on fertility and reproductive performance in rats (6.9 and 3.0 mg/kg/day in males and females, respectively) were associated with plasma fenfluramine exposures (AUC) approximately 3 and 0.6 times, respectively, and norfenfluramine exposures approximately 5 and 3 times, respectively, those in humans at the MRHD.

14 CLINICAL STUDIES

14.1 Dravet Syndrome

The effectiveness of FINTEPLA for the treatment of seizures associated with DS in patients 2 years of age and older was established in two randomized, double-blind, placebo-controlled trials in patients 2 to 18 years of age.

Study 1 (N=117) compared a 0.7 mg/kg/day and a 0.2 mg/kg/day dose of FINTEPLA with placebo in patients who were not receiving stiripentol (NCT02682927 and NCT02826863). Study 2 (N=85) compared a 0.4 mg/kg/day dose of FINTEPLA with placebo in patients who were receiving stiripentol and either clobazam, valproate, or both (NCT02926898). In both studies, patients had a clinical diagnosis of DS and were inadequately controlled on at least one AED or other antiseizure treatment including vagal nerve stimulation or a ketogenic diet. Both trials had a 6-week baseline period, during which patients were required to have a minimum of 6 convulsive seizures while on stable AED therapy. Convulsive seizures included tonic, clonic, generalized tonic-clonic, tonic-atonic, secondarily generalized tonic-clonic, hemiclonic, and focal with observable motor signs. The baseline period was followed by randomization into a 2- week (Study 1) or 3-week (Study 2) titration period and a subsequent 12-week maintenance period, where the dose of FINTEPLA remained stable.

In Study 1, 98% of patients were taking between 1 and 4 concomitant AEDs. The most frequently used concomitant AEDs (in at least 25% of patients), were valproate (61%), clobazam (59%), and topiramate (25%). In Study 2, 100% of patients were taking between 2 and 4 concomitant AEDs. The most frequently used concomitant AEDs (in at least 25% of patients), were stiripentol (100%), clobazam (94%), and valproate (89%).

The primary efficacy endpoint in both studies was the change from baseline in the frequency of convulsive seizures per 28 days during the combined 14-week (Study 1) or 15-week (Study 2) titration and maintenance periods (i.e., treatment period). The median longest interval between convulsive seizures was also assessed.

In Study 1 and Study 2, the reduction in convulsive seizure frequency per 28 days was statistically significantly greater for all dose groups of FINTEPLA compared to placebo (Table 6). A reduction in convulsive seizures was observed within 3 to 4 weeks of starting FINTEPLA, and the effect remained generally consistent over the 14- or 15-week treatment period.

Table 6: Change in Convulsive Seizure Frequency During the Treatment Period in Patients with Dravet Syndrome (Study 1 and Study 2)
Convulsive Seizure Frequency (per 28 days) | Placebo | FINTEPLA 0.2 mg/kg/day | FINTEPLA 0.7 mg/kg/day | FINTEPLA 0.4 mg/kg/day
Study 1 | N=39 | N=38 | N=40 | NA
Baseline Period Median | 29.4 | 18.1 | 18.7 | NA
% Difference Relative to Placebo [Derived from the primary analysis model] |  | -31.7% | -70.0% | NA
p-value compared to placebo |  | 0.043 | <0.001
Study 2 | N=42 | NA | NA | N=43
Baseline Period Median | 11.5 | NA | NA | 15.0
% Difference Relative to Placebo |  | NA | NA | -59.5%
p-value compared to placebo |  |  |  | <0.001
±All 0.4 mg/kg/day patients were also taking concomitant stiripentol, which increases the exposure of FINTEPLA.

Figure 1 and Figure 2 display the percentage of patients by category of seizure response from baseline in convulsive seizure frequency (per 28 days) during the treatment period in Study 1 and Study 2, respectively.

Figure 1: Proportion of Patients by Category of Seizure Response for FINTEPLA and Placebo in Patients with Dravet Syndrome (Study 1)

Figure 2: Proportion of Patients by Category of Seizure Response for FINTEPLA and Placebo in Patients with Dravet Syndrome (Study 2)

In Study 1, 3 of 40 (8%) patients in the FINTEPLA 0.7 mg/kg/day group and 3 of 38 (8%) patients in the FINTEPLA 0.2 mg/kg/day group reported no convulsive seizures during the 14-week treatment period, compared to 0 patients in the placebo group. In Study 2, 1 of 43 (2%) patients in the FINTEPLA 0.4 mg/kg/day group reported no convulsive seizures during the 15-week treatment period, compared to 0 patients in the placebo group.

In Study 1 and Study 2, FINTEPLA was associated with a statistically significant longer interval between convulsive seizures compared to placebo (Figure 3).

Figure 3: Median Longest Interval Between Convulsive Seizures in Patients with Dravet Syndrome (Study 1 and Study 2)

14.2 Lennox-Gastaut Syndrome

The effectiveness of FINTEPLA for the treatment of seizures associated with LGS in patients 2 years of age and older was established in a randomized, double-blind, placebo-controlled study in 263 patients 2 to 35 years of age (Study 3; NCT03355209).

Study 3 compared a 0.7 mg/kg/day and a 0.2 mg/kg/day dose of FINTEPLA with placebo. Patients had a diagnosis of LGS and were inadequately controlled on at least one AED, with or without vagal nerve stimulation and/or ketogenic diet. The study had a 4-week baseline period, during which patients were required to have a minimum of 8 drop seizures while on stable AED therapy. Drop seizures were generalized tonic-clonic, secondarily generalized tonic-clonic, tonic, atonic, or tonic-atonic seizures that were confirmed to result in drops. The baseline period was followed by randomization into a 2-week titration period and a subsequent 12-week maintenance period, where the dose of FINTEPLA remained stable.

In Study 3, 99% of patients were taking between 1 and 4 concomitant AEDs. The most frequently used concomitant AEDs (in at least 25% of patients) were clobazam (45%), lamotrigine (34%), and valproate (56%).

The primary efficacy endpoint in Study 3 was the median percent change from baseline in the frequency of drop seizures per 28 days during the combined 14-week titration and maintenance periods (i.e., treatment period). The proportion of patients who achieve improvement (minimally, much, or very much improved) in the Clinical Global Impression of Change (CGI-I) as assessed by Principal Investigator was a secondary endpoint.

In Study 3, the median percent change from baseline (reduction) in the frequency of drop seizures per 28 days was significantly greater for the 0.7 mg/kg/day dose group of FINTEPLA compared with placebo (Table 7). A reduction in drop seizures was observed within 2 weeks of initiating treatment with FINTEPLA, and the effect remained generally consistent over the 14-week treatment period.

The median percent reduction from baseline in drop seizure frequency per 28 days for the lower dose of FINTEPLA (0.2 mg/kg/day) did not reach statistical significance compared to placebo (Table 7).

Table 7: Change in Drop Seizure Frequency during the Treatment Period in Patients with Lennox-Gastaut Syndrome (Study 3)
Drop Seizure Frequency (per 28 days) | Placebo | FINTEPLA 0.2 mg/kg/day | FINTEPLA 0.7 mg/kg/day
Study 3 | N=85 [The total number of patients upon which the efficacy analysis was based is less than the total number randomized in the double-blind, placebo-controlled study because patients with missing data were excluded from the efficacy analysis.] | N=86 | N=83
Baseline Period Median Seizure Frequency | 55.0 | 77.8 | 80.0
Median Percentage Change from Baseline During Treatment | -8.7% | -13.2% | -23.7%
p-value compared to placebo |  | 0.1917 [Not statistically significant] | 0.0037

Figure 4 displays the percentage of patients by category of reduction from baseline in drop seizure frequency per 28 days during the treatment period in Study 3.

Figure 4: Proportion of Patients by Category of Seizure Response for FINTEPLA and Placebo in Patients with Lennox–Gastaut Syndrome (Study 3)

Numerically greater improvements on the CGI-I by Investigator were observed in patients treated with FINTEPLA compared with placebo.

16 HOW SUPPLIED/STORAGE AND HANDLING

16.1 How Supplied

FINTEPLA oral solution is a clear, colorless, cherry flavored liquid containing 2.2 mg/mL fenfluramine and is supplied in a white plastic bottle with a child resistant closure as follows:

- Carton containing one 360 mL bottle (NDC 43376-322-36)
- Carton containing one 30 mL bottle (NDC 43376-322-30)

Before dispensing, the pharmacist will insert a press-in bottle adapter into the dispensing bottle. The pharmacy will provide 3 mL or 6 mL calibrated oral dosing syringes.

16.2 Storage and Handling

Store FINTEPLA at room temperature between 20°C to 25°C (68°F to 77°F); excursions are permitted between 15°C to 30°C (59°F to 86°F) [see USP Controlled Room Temperature].

Do not refrigerate or freeze. Store the bottle and syringe together.

Discard any unused portion 3 months after first opening the bottle or the "Discard After" date on the bottle, whichever is sooner.

17 PATIENT COUNSELING INFORMATION

Advise the patient to read the FDA-approved patient labeling (Medication Guide and Instructions for Use).

Administration Information

Advise patients who are prescribed FINTEPLA to use the oral dosing syringes provided by the pharmacy [see Dosage and Administration (2.7)and Instructions for Use] . Instruct patients to discard any unused FINTEPLA 3 months after first opening the bottle or if the "discard after" date on the dispensing bottle has passed, whichever is sooner [see How Supplied/Storage and Handling (16.1), (16.2)].

Valvular Heart Disease and Pulmonary Arterial Hypertension

Advise patients that cardiac monitoring must be performed using echocardiography to monitor for serious heart valve changes or high blood pressure in the arteries of the lungs [see Warnings and Precautions (5.1)].

FINTEPLA REMS Program

FINTEPLA is available only through a restricted program called the FINTEPLA REMS program [see Warnings and Precautions (5.2)] . Inform the patient of the following notable requirements:

- Patients must enroll in the program and comply with ongoing echocardiogram monitoring requirements [see Warnings and Precautions (5.1)].

FINTEPLA is only prescribed by certified health care providers and only dispensed from certified pharmacies participating in the program. Therefore, provide patients with the telephone number and website for information on how to obtain the product [see Warnings and Precautions (5.2)].

Decreased Appetite and Decreased Weight

Advise patients that decreased appetite is frequent during treatment with FINTEPLA, which can cause decrease in weight [see Warnings and Precautions (5.3)] .

Somnolence, Sedation, and Lethargy

Inform patients that FINTEPLA can cause somnolence, sedation, and lethargy. Caution patients about operating hazardous machinery, including motor vehicles, until they are reasonably certain that FINTEPLA does not affect them adversely (e.g., impair judgment, thinking, or motor skills) [see Warnings and Precautions (5.4)] .

Suicidal Thinking and Behavior

Counsel patients, their caregivers, and their families that antiepileptic drugs may increase the risk of suicidal thoughts and behavior and advise them to be alert for the emergence or worsening of symptoms of depression, any unusual changes in mood or behavior, or the emergence of suicidal thoughts, behavior, or thoughts of self-harm. Instruct patients, caregivers, and families to report behaviors of concern immediately to healthcare providers [see Warnings and Precautions (5.5)] .

Withdrawal of Antiepileptic Drugs (AEDs)

Advise patients not to discontinue use of FINTEPLA without consulting with their healthcare provider. FINTEPLA should normally be gradually withdrawn to reduce the potential for increased seizure frequency and status epilepticus [see Dosage and Administration (2.8), Warnings and Precautions (5.6)] .

Serotonin Syndrome

Inform patients about the risk of serotonin syndrome, which can be life-threatening. Advise patients on the signs and symptoms of serotonin syndrome and that certain over-the-counter medications and herbal supplements can increase this risk [see Warnings and Precautions (5.7)].

Increase in Blood Pressure

Inform patients that FINTEPLA can cause an increase in blood pressure [see Warnings and Precautions (5.8)].

Glaucoma

Inform patients that FINTEPLA can cause mydriasis and can precipitate angle closure glaucoma. Instruct patients to contact their healthcare provider if they have any acute decreases in visual acuity or ocular pain [see Warnings and Precautions (5.9)].

Pregnancy Registry

Advise patients to notify their healthcare provider if they become pregnant or intend to become pregnant during FINTEPLA therapy. Encourage women who are taking FINTEPLA to enroll in the North American Antiepileptic Drug (NAAED) Pregnancy Registry if they become pregnant. This registry is collecting information about the safety of antiepileptic drugs during pregnancy [see Use in Specific Populations (8.1)] .

Manufactured for:
UCB, Inc.
1950 Lake Park Drive
Smyrna, GA 30080

FINTEPLA®is a registered trademark of the UCB Group of Companies.

©2025 UCB, Inc., Smyrna, GA 30080.
All rights reserved.

MEDICATION GUIDE
FINTEPLA®(fin-TEP-la)
(fenfluramine)
oral solution

Read this Medication Guide before you start taking FINTEPLA and each time you get a refill. There may be new information. This information does not take the place of talking to your healthcare provider about your medical condition or treatment.

What is the most important information I should know about FINTEPLA?
FINTEPLA can cause serious side effects, including:

- Problems with the valves in the heart (valvular heart disease) and high blood pressure in the arteries of the lungs (pulmonary arterial hypertension)have been associated with FINTEPLA. Your healthcare provider will do a test called an echocardiogram to check your heart and for high blood pressure in the arteries of the lungs before you start taking FINTEPLA, again every 6 months during treatment, and one time 3 to 6 months after you take your last dose of FINTEPLA.
  Call your healthcare provider right away if you develop any of these signs and symptoms of heart or lung problems during treatment with FINTEPLA:

- shortness of breath
- tiredness or weakness, especially with increased activity
- lightheadedness or fainting
- swollen ankles or feet

- chest pain
- sensations of a rapid, fluttering heartbeat (palpitations)
- irregular pulse
- bluish color to your lips and skin (cyanosis)

Because of the risk of heart valve problems (valvular heart disease) and high blood pressure in arteries of lungs (pulmonary arterial hypertension) FINTEPLA is only available through a restricted program called the FINTEPLA Risk Evaluation and Mitigation Strategy (REMS) Program. Before you or your child receives FINTEPLA, your healthcare provider or pharmacist will make sure you understand how to take FINTEPLA safely. If you have any questions about FINTEPLA, ask your healthcare provider, visit www.FinteplaREMS.com, or call 1-877-964-3649.

- Decreased appetite and decreased weight.Decreased appetite and decreased weight are both serious and common side effects of FINTEPLA in people with Dravet syndrome (DS) or Lennox-Gastaut syndrome (LGS).
  - Your weight should be checked regularly during your treatment with FINTEPLA.
  - Your healthcare provider may need to make changes to your FINTEPLA dose if your weight decreases. In some cases, FINTEPLA may need to be stopped.
- Sleepiness, sedation, and lack of energy (lethargy).These are both serious and common side effects of FINTEPLA in people with Dravet syndrome (DS) or Lennox-Gastaut syndrome (LGS). Taking FINTEPLA with central nervous system (CNS) depressants including alcohol may increase sleepiness. Do notdrive, operate heavy machinery, or do other dangerous activities until you know how FINTEPLA affects you.
- Like all other antiepileptic drugs, FINTEPLA may cause suicidal thoughts or actionsin a very small number of people (about 1 in 500).
  Call your healthcare provider right away if you have any of these symptoms, especially if they are new, worse, or worry you:

- thoughts about suicide or dying
- trouble sleeping (insomnia)
- attempts to commit suicide
- new or worse irritability
- new or worse depression
- acting aggressive, being angry, or violent

- new or worse anxiety
- acting on dangerous impulses
- feeling agitated or restless
- an extreme increase in activity and talking (mania)
- panic attacks
- other unusual changes in behavior or mood

How can I watch for early symptoms of suicidal thoughts and actions?

- Pay attention to any changes, especially sudden changes, in mood, behaviors, thoughts, or feelings.
- Keep all follow-up visits with your healthcare provider as scheduled.

Suicidal thoughts or actions can be caused by things other than medicines. If you have suicidal thoughts or actions, your healthcare provider may check for other causes.

- Do not stop taking FINTEPLA without first talking to your healthcare provider. Stopping a seizure medicine such as FINTEPLA suddenly can cause you to have seizures more often or seizures that do not stop (status epilepticus).

Call your healthcare provider between visits as needed, especially if you are worried about symptoms.

What is FINTEPLA?

- FINTEPLA is a prescription medicine used to treat the seizures associated with Dravet syndrome (DS) and Lennox- Gastaut syndrome (LGS) in patients 2 years of age and older.
- It is not known if FINTEPLA is safe and effective in children less than 2 years of age.

Do not take FINTEPLA if you:

- are allergic to fenfluramine or any of the ingredients in FINTEPLA. See the end of this Medication Guide for a complete list of ingredients in FINTEPLA.
- are taking or have stopped taking medicines called monoamine oxidase inhibitors (MAOI) in the last 14 days. This may cause a serious or life-threatening problem called serotonin syndrome.If you are not sure whether or not you are taking one of these medicines, contact your healthcare provider.

Before taking FINTEPLA, tell your healthcare provider about all of your medical conditions, including if you:

- have heart problems
- have or have had weight loss
- have or have had depression, mood problems, or suicidal thoughts or behavior
- have kidney problems
- have liver problems
- are pregnant or plan to become pregnant. Tell your healthcare provider right away if you become pregnant while taking FINTEPLA. You and your healthcare provider will decide if you should take FINTEPLA while you are pregnant.
  - If you become pregnant while taking FINTEPLA, talk to your healthcare provider about registering with the North American Antiepileptic Drug Pregnancy Registry. You can enroll in this registry by calling 1-888-233-2334 or go to www.aedpregnancyregistry.org. The purpose of this registry is to collect information about the safety of antiepileptic drugs during pregnancy.
- are breastfeeding or plan to breastfeed. It is not known if FINTEPLA passes into your breast milk. Talk to your healthcare provider about the best way to feed your baby while taking FINTEPLA.

Tell your healthcare provider about all the medicines you take,including prescription and over-the-counter medicines, vitamins, and herbal supplements.
Know the medicines you take. Keep a list of them to show your healthcare provider or pharmacist when you get a new medicine.

How should I take FINTEPLA?

- Read the Instructions for Useat the end of this Medication Guide for information on the right way to use FINTEPLA.
- Take FINTEPLA exactly as your healthcare provider tells you to take it.
- Your healthcare provider will tell you how much FINTEPLA to take and when to take it.
- FINTEPLA may be taken with or without food.
- Measure your dose of FINTEPLA using the dosing syringe that is provided by the pharmacy. Do not use a household teaspoon or tablespoon.
- FINTEPLA can be given through gastric and nasogastric feeding tubes

What should I avoid while taking FINTEPLA?

- Do notdrive, operate heavy machinery, or do other dangerous activities until you know how FINTEPLA affects you. FINTEPLA may cause you to feel sleepy.

What are the possible side effects of FINTEPLA?
FINTEPLA may cause serious side effects, including:

- See " What is the most important information I should know about FINTEPLA?"
- serotonin syndrome.Serotonin syndrome is a life-threatening problem that can happen in people taking FINTEPLA, especially if FINTEPLA is taken with certain other medicines to include:

- anti-depressant medicines called SSRIs, SNRIs, TCAs, and MAOIs
- tryptophan
- lithium
- antipsychotics

- St. John's Wort
- dextromethorphan
- tramadol

Call your healthcare provider right away if you have any of the following symptoms of serotonin syndrome.

- mental status changes such as seeing things that are not there (hallucinations), agitation, or coma
- changes in blood pressure
- tight muscles

- fast heartbeat
- nausea, vomiting, diarrhea
- high body temperature
- trouble walking

- high blood pressure (hypertension).Hypertension is both a serious and common side effect. FINTEPLA can cause your blood pressure to increase even if you have never had high blood pressure before. Your healthcare provider will check your blood pressure while you are taking FINTEPLA.
- increased pressure in your eye (glaucoma).Symptoms of glaucoma may include:

- red eyes
- seeing halos or bright colors around lights
- nausea or vomiting

- decreased vision
- eye pain or discomfort
- blurred vision

If you have any of these symptoms, call your healthcare provider right away.
The most common side effects of FINTEPLA when used to treat Dravet syndrome (DS) include:

- decreased appetite
- diarrhea
- low energy
- respiratory infection
- decreased weight
- fever
- constipation
- abnormal echocardiogram

- sleepiness
- problems with movement, balance, and walking
- increased drooling
- increased blood pressure
- vomiting
- falls
- seizures that do not stop
- weakness

The most common side effects of FINTEPLA when used to treat Lennox-Gastaut syndrome (LGS) include:

- diarrhea
- tiredness
- vomiting

- sleepiness
- decreased appetite

These are not all the possible side effects of FINTEPLA. For more information, ask your healthcare provider or pharmacist.
Tell your healthcare provider if you have any side effect that bothers you or that does not go away.
Call your doctor for medical advice about side effects. You may report side effects to FDA at 1-800-FDA-1088.

How should I store FINTEPLA?

- Store FINTEPLA at room temperature between 68°F to 77°F (20°C and 25°C).
- Do notrefrigerate or freeze.
- Store the FINTEPLA bottle and syringe together in a clean area.
- Throw away (discard) any unused FINTEPLA 3 months after first opening the bottle or if the Discard After date on the package or bottle has passed. Whichever one comes first.

Keep FINTEPLA and all medicines out of the reach of children.

General information about the safe and effective use of FINTEPLA.
Medicines are sometimes prescribed for purposes other than those listed in a Medication Guide. Do not use FINTEPLA for a condition for which it was not prescribed. Do not give FINTEPLA to other people, even if they have the same symptoms that you have. It may harm them.
You can ask your pharmacist or healthcare provider for information about FINTEPLA that is written for health professionals.

What are the ingredients in FINTEPLA?
Active ingredient:fenfluramine hydrochloride
Inactive ingredients: cherry flavor, citric acid, ethylparaben, hydroxyethylcellulose, methylparaben, potassium citrate, sucralose, and water.
FINTEPLA contains no ingredient made from gluten-containing grain (wheat, barley, or rye) and contains not more than 0.1% of carbohydrates, which is from the cherry flavoring.
Manufactured for: UCB, Inc., Smyrna, GA 30080
FINTEPLA®is a registered trademark of the UCB Group of Companies. ©2025. All rights reserved.
For more information about FINTEPLA, go to www.fintepla.com or call 1-844-599-2273.

This Medication Guide has been approved by the U.S. Food and Drug Administration.

Revised: 4/2025

INSTRUCTIONS FOR USE FINTEPLA®(fin-TEP-la) (fenfluramine) oral solution 2.2 mg/mL

Be sure that you read, understand, and follow these instructions before you start using FINTEPLA oral solution and each time you get a refill. There may be new information.

This Instructions for Use contains information on how to take FINTEPLA. This information does not take the place of talking to your healthcare provider about your medical condition or treatment.

What is included with FINTEPLA?

The following items are included to prepare and give an oral dose of FINTEPLA:

- 1 bottle of FINTEPLA oral solution (2.2 mg/mL)
- 2 reusable oral syringes
  1 Bottle of FINTEPLA Oral Solution (2.2 mg/mL)
  2 Oral Syringes

Call the pharmacist at 1-844-288-5007 if you did not receive the items listed above, or if you need help using them.

Important information about FINTEPLA

- FINTEPLA is an oralmedicine (taken by mouth) and is given 2 times each day. Follow your healthcare provider's instructions for taking or giving doses of FINTEPLA.
- If you have questions about how to prepare or give FINTEPLA, contact your healthcare provider or call your pharmacist.
- Always use the oral syringes provided with FINTEPLA to make sure the right dose is given. If you need a new syringe contact your pharmacist. Do notuse a household teaspoon or tablespoon.

Oral syringes provided with FINTEPLA by the pharmacy.

With FINTEPLA you will receive 2 reusable oral syringes.

2 oral syringes that can measure up to 3 mL

OR

2 oral syringes that can measure up to 6 mL

or

Call the pharmacist at 1-844-288-5007 if you have any questions about the syringes provided with FINTEPLA.

Parts of the Oral Syringe

Preparing a Dose

Step 1.Make sure you have:

- The bottle of FINTEPLA oral solution, and
- A clean, dry reusable oral syringe that was provided with FINTEPLA.

Step 2.Check the "Discard After" date (MM/DD/YYYY).

- Do notuse the medicine if the "Throw Away" (Discard) date has passed.
- If the date is near, contact your pharmacy or healthcare provider to get a refill or new prescription.
- If the date has passed, dispose of any unused FINTEPLA.

Step 3.Press down and turn the childproof cap to the left (counterclockwise) and remove it from the bottle.

- Set the cap aside (do not throw away).

Step 4.Make sure the adapter is on the bottle.

- If the bottle does not have an adapter, contact the pharmacist.
- Always leave the adapter in placein the bottle of medicine.

Step 5.Remove an oral syringe from its packaging, if needed.
Only use the oral syringes provided with FINTEPLA.
If an oral syringe is damaged, or you cannot read the dose markings:

- Use the other oral syringe provided, or
- Contact the pharmacist to get a new one.

Step 6.Make sure the plunger is pushed all the way into the oral syringe.

Step 7.Hold the bottle of medicine firmly on a hard, flat surface.
Step 8.Push the tip of the oral syringe into the opening of the adapter until it cannot be pushed further.

Step 9.Hold the oral syringe and bottle together and turn upside down.

Step 10.Slowly pull the plunger of the oral syringe to withdraw the prescribed dose.

Step 11.Line up the end of the plunger with the mark for the prescribed dose on the oral syringe.
Tips to Getting the Correct Dose

- If you draw out too much medicine:
  - Leave the oral syringe in the adapter.
  - Push the plunger slowly back into the syringe until you reach the prescribed dose.
- If you see air bubbles in the medicine:
  - Leave the oral syringe in the adapter.
  - Pull the plunger further down.
  - Allow the bubbles to rise to the tip of the syringe.
  - Push the plunger in all the way.
  - Slowlypull the plunger out to the prescribed dose.
    Note:Very small bubbles in the liquid are normal.

Step 12.Hold the oral syringe and bottle together and then turn the bottle right side up.

Step 13.Holding the bottle firmly, gently pull the oral syringe out of the bottle adapter.

Step 14.Make sure the dose in the oral syringe still matches the prescribed dose.
If the dose does not match:

- Put the syringe back into adapter.
- See steps 9 to 11 to adjust the dose, as needed.

Giving FINTEPLA

Step 15.Place the tip of the oral syringe against the inside of the cheek.
Step 16.Gently push the plunger in until all the medicine in the oral syringe is given.

- Do notsquirt or forcefully push the medicine into the back of the throat. This may cause choking.

Step 17.Place the cap back on the bottle tightly by turning the cap right (clockwise) until it stops.

- Always leave the adapter in place in the bottle
- The cap will fit over it.

Cleaning the syringe

- Rinse the oral syringe with cold water and allow it to air dry after each use.
- Make sure you rinse the inside of the syringe and the plunger.

Cleaning Tips:

- Pull cold water into the syringe with the plunger and push it out several times to clean the syringe.
- Remove the plunger from the barrel of the oral syringe.
- Rinse both parts under cold water.
- Make sure the syringe and plunger are completely dry before the next use.
- Do not use detergent to clean the syringe and plunger.
- Do not clean in the dishwasher.

How should I store FINTEPLA?

- Store FINTEPLA at room temperature between 68°F to 77°F (20°C to 25°C).
- Do notrefrigerate or freeze.
- Keep the cap tightly closed and the bottle upright.
- Store the FINTEPLA bottle and syringe together in a clean area.
- Throw away (discard) any unused FINTEPLA 3 months after first opening the bottle orif the Discard After date on the package or bottle has passed. Whichever one comes first.
- Keep FINTEPLA and all medicines out of the reach of children.

Manufactured for: UCB, Inc., Smyrna, GA 30080

FINTEPLA®is a registered trademark of the UCB Group of Companies. ©2025. All rights reserved.

This Instructions for Use has been approved by the U.S. Food and Drug Administration.
Revised: 10/2025

PRINCIPAL DISPLAY PANEL - 30 mL Bottle Label - NDC 3376-322-30

NDC 43376-322-30

Fintepla®
(fenfluramine)
oral solution
2.2 mg/mL

Rx only
For oral use only

Contents 30 mL

PRINCIPAL DISPLAY PANEL - 30 mL Bottle Carton - NDC 3376-322-30

NDC 43376-322-30

Fintepla®
(fenfluramine)
oral solution
2.2 mg/mL

For oral use only

Attention Pharmacist:
Dispense the enclosed
Medication Guide to each patient

Contents:
One 30 mL bottle

Rx only

PRINCIPAL DISPLAY PANEL - 360 mL Bottle Label - NDC 43376-322-36

NDC 43376-322-36

Fintepla®
(fenfluramine)
oral solution
2.2 mg/mL

For oral use only

Rx only

Contents 360 mL

PRINCIPAL DISPLAY PANEL - 360 mL Bottle Carton - NDC 43376-322-36

Fintepla®
(fenfluramine)
oral solution
2.2 mg/mL

For oral use only

Attention Pharmacist:
Dispense the enclosed
Medication Guide to each
patient

Contents:
One 360 mL bottle

Rx only